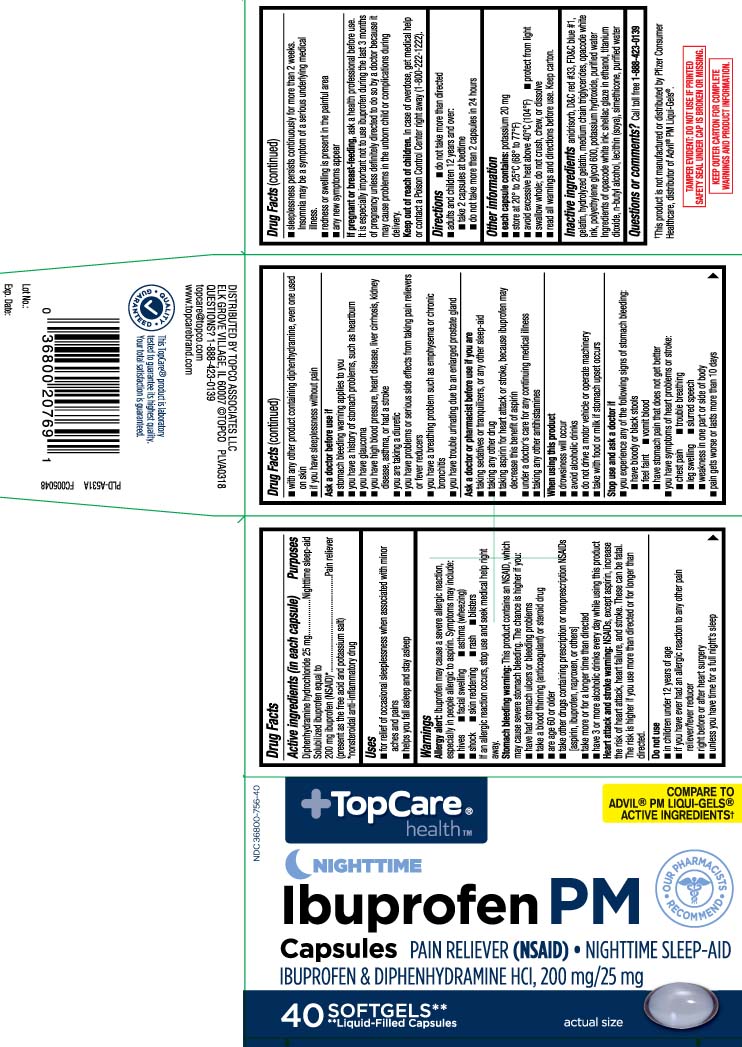 DRUG LABEL: Ibuprofen PM
NDC: 36800-756 | Form: CAPSULE, LIQUID FILLED
Manufacturer: TOP CARE (Topco Associates LLC)
Category: otc | Type: HUMAN OTC DRUG LABEL
Date: 20221128

ACTIVE INGREDIENTS: IBUPROFEN 200 mg/1 1; DIPHENHYDRAMINE HYDROCHLORIDE 25 mg/1 1
INACTIVE INGREDIENTS: FD&C BLUE NO. 1; D&C RED NO. 33; GELATIN; POLYETHYLENE GLYCOL 600; POTASSIUM HYDROXIDE; WATER; SORBITAN; SORBITOL; MEDIUM-CHAIN TRIGLYCERIDES

Drug Facts

Active ingredient (in each capsule)

Diphenhydramine hydrochloride 25 mg

Solubilized ibuprofen equal to 200 mg ibuprofen (NSAID)*
(present as the free acid and potassium salt)
*non-steroidal anti-inflammatory drug

Purpose

Nighttime sleep-aid

Pain Reliever

Uses

- for relief of occasional sleeplessness when associated with minor aches and pains
- helps you fall asleep and stay asleep

Warnings

Allergy alert: Ibuprofen may cause a severe allergic reaction, especially in people allergic to aspirin. Symptoms may include:

- hives
- facial swelling
- asthma (wheezing)
- shock
- skin reddening
- rash
- blisters

If an allergic reaction occurs, stop use and seek medical help right away.

Stomach bleeding warning: This product contains an NSAID, which may cause severe stomach bleeding. The chance is higher if you:

- have had stomach ulcers or bleeding problems
- take a blood thinning (anticoagulant) or steroid drug
- are age 60 or older
- take other drugs containing prescription or nonprescription NSAIDs [aspirin, ibuprofen, naproxen, or others]
- take more or for a longer time than directed
- have 3 or more alcoholic drinks every day while using this product

Heart attack and stroke warning: NSAIDs, except aspirin, increase the risk of heart attack, heart failure, and stroke. These can be fatal. The risk is higher if you use more than directed or for longer than directed.

Do not use

- in children under 12 years of age
- if you have ever had an allergic reaction to any other pain reliever/fever reducer
- right before or after heart surgery
- unless you have time for a full night’s sleep
- with any other product containing diphenhydramine, even one used on skin
- if you have sleeplessness without pain

Ask a doctor before use if

- the stomach bleeding warning applies to you
- you have a history of stomach problems, such as heartburn
- you have glaucoma
- you have high blood pressure, heart disease, liver cirrhosis, kidney disease, asthma or had a stroke
- you are taking a diuretic
- you have problems or serious side effects from taking pain relievers or fever reducers
- you have a breathing problem such as emphysema or chronic bronchitis
- you have trouble urinating due to an enlarged prostate gland

Ask a doctor or pharmacist before use if you are

- taking sedatives or tranquilizers, or any other sleep-aid
- taking any other drug
- taking any other antihistamines
- taking aspirin for heart attack or stroke, because ibuprofen may decease this benefit of aspirin
- under a doctor's care for any continuing medical illness

When using this product

- drowsiness will occur
- avoid alcoholic drinks
- do not drive a motor vehicle or operate machinery
- take with food or milk if stomach upset occurs

Stop use and ask a doctor if

- you experience any of the following signs of stomach bleeding:
  - feel faint
  - have bloody or black stools
  - vomit blood
  - have stomach pain that does not get better
- you have symptoms of heart problems or stroke:
  - chest pain
  - trouble breathing
  - leg swelling
  - slurred speech
  - weakness in one part or side of body
- pain gets worse or last more than 10 days
- sleeplessness persists continuously for more than 2 weeks. Insomnia may be a symptom of a serious underlying medical illness
- redness or swelling is present in the painful area
- any new symptoms appear

If pregnant or breast-feeding,

ask a health professional before use. It is especially important not to use ibuprofen during the last 3 months of pregnancy unless definitely directed to do so by a doctor because it may cause problems in the unborn child or complications during delivery.

Keep out of reach of children.

In case of overdose, get medical help or contact a Poison Control Center right away (1-800-222-1222).

Directions

- do not take more than directed
- adults and childlren 12 years and over:
  - take 2 capsules at bedtime
  - do not take more than 2 capsules in 24 hours

Other information

- each capsule contains: potassium 20 mg
- store at 20º to 25ºC (68º to 77ºF)
- avoid excessive heat above 40°C (104°F)
- protect from light
- swallow whole: do not crush, chew, or dissolve
- read all warnings and directions before use. Keep carton.

Inactive ingredients

D&C red #33, FD&C blue #1, gelatin, medium chain triglycerides, polyethylene glycol 600, potassium hydroxide, purified water, sorbitan, sorbitol

Questions or comments?

Call toll free 1-888-423-0139

Principal Display Panel

COMPARE TO ADVIL®PM LIQUI-GELS® ACTIVE INGREDIENTS†

NIGHTTIME

Ibuprofen PM Capsules

PAIN RELIEVER (NSAID) • NIGHTTIME SLEEP-AID

IBUPROFEN & DIPHENHYDRAMINE HCI 200 mg/25mg

SOFTGELS**

**Liquid-Filled Capsules

†This product is not manufactured or distributed by Pfizer Consumer Healthcare, distributor of Advil® PM Liqui-Gels®.

TAMPER EVIDENT: DO NOT USE IF PRINTED SAFETY SEAL UNDER CAP IS BROKEN OR MISSING.

KEEP OUTER CARTON FOR COMPLETE WARNINGS AND PRODUCT INFORMATION.

DISTRIBUTED BY TOPCO ASSOCIATES LLC

ELK GROVE VILLAGE, IL 60007

©TOPCO PLVA0318

topcare@topco.com

www.topcarebrand.com

Product Packaging

TOPCARE Ibuprofen 200 mg Softgels